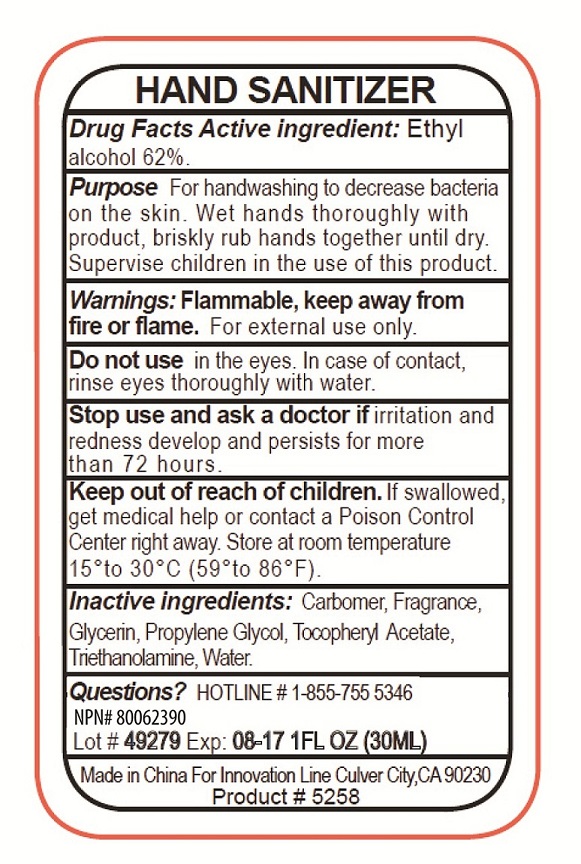 DRUG LABEL: ANTISEPTIC HAND SANITIZER
NDC: 76138-113 | Form: GEL
Manufacturer: Innovation Specialties Inc
Category: otc | Type: HUMAN OTC DRUG LABEL
Date: 20240710

ACTIVE INGREDIENTS: ALCOHOL 62 mL/100 mL
INACTIVE INGREDIENTS: CARBOMER HOMOPOLYMER, UNSPECIFIED TYPE; GLYCERIN; PROPYLENE GLYCOL; .ALPHA.-TOCOPHEROL ACETATE; TROLAMINE; WATER

ANTISEPTIC HAND SANITIZER

Active ingredient

Ethyl alcohol 62%

Purpose

Antiseptic

Keep out of reach of children.If swallowed, get medical help or contact a Poison Control Center right away.

Use

For handwashing to decrease bacteria on the skin.

Warnings

Flammable, keep away from fire or flame.For external use only.

Do not usein the eyes. In case of contact, rinse eyes thoroughly with water.

Stop use and ask a doctor ifirritation and redness develop and persist for more than 72 hours.

Directions

Wet hands thoroughly with product, briskly rub hands together until dry. Supervise children in the use of this product.

Inactive ingredients

Carbomer, Fragrance, Glycerin, Propylene Glycol, Tocopheryl Acetate, Triethanolamine, Water.

STORAGE AND HANDLING

Store at room temperature 15^0to 30^0C (59^0to 86^0F)

Questions?

HOTLINE # 1-855-755-5346

Made in China for Innovation Line Culver City, CA 90230